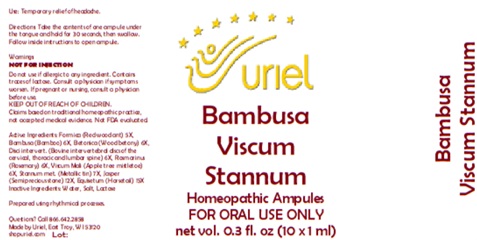 DRUG LABEL: Bambusa Viscum Stannum
NDC: 48951-2023 | Form: LIQUID
Manufacturer: Uriel Pharmacy Inc.
Category: homeopathic | Type: HUMAN OTC DRUG LABEL
Date: 20251114

ACTIVE INGREDIENTS: FORMICA RUFA 5 [hp_X]/1 mL; BAMBUSA VULGARIS WHOLE 6 [hp_X]/1 mL; STACHYS OFFICINALIS 6 [hp_X]/1 mL; BOS TAURUS INTERVERTEBRAL DISC 6 [hp_X]/1 mL; ROSMARINUS OFFICINALIS FLOWERING TOP 6 [hp_X]/1 mL; VISCUM ALBUM FRUITING TOP 6 [hp_X]/1 mL; TIN 7 [hp_X]/1 mL; SILICON DIOXIDE 12 [hp_X]/1 mL; EQUISETUM ARVENSE TOP 15 [hp_X]/1 mL
INACTIVE INGREDIENTS: WATER; SODIUM CHLORIDE; LACTOSE

Bambusa Viscum Stannum

PURPOSE

Use: Temporary relief of headache.

INDICATIONS AND USAGE

FOR ORAL USE ONLY

DOSAGE AND ADMINISTRATION

Directions: Take the contents of one ampule under the tongue and hold for 30 seconds, then swallow. Follow inside instructions to open ampule.

Warnings:
NOT FOR INJECTION
Do not use if allergic to any ingredient. Contains traces of lactose. Consult a physician if symptoms worsen. If pregnant or nursing, consult a physician before use.
Claims based on traditional homeopathic practice, not accepted medical evidence. Not FDA evaluated.

KEEP OUT OF REACH OF CHILDREN.

ACTIVE INGREDIENT

Active Ingredients: Formica (Red wood ant) 5X, Bambusa (Bamboo) 6X, Betonica (Wood betony) 6X, Disci intervert. (Bovine intervertebral discs of the cervical, thoracic and lumbar spine) 6X, Rosmarinus (Rosemary) 6X, Viscum Mali (Apple tree mistletoe) 6X, Stannum met. (Metallic tin) 7X, Jasper (Semiprecious stone) 12X, Equisetum (Horsetail) 15X

Inactive Ingredients: Water, Salt, Lactose

Prepared using rhythmical processes.

Questions? Call 866.642.2858
Made by Uriel, East Troy, WI 53120
shopuriel.com Lot: